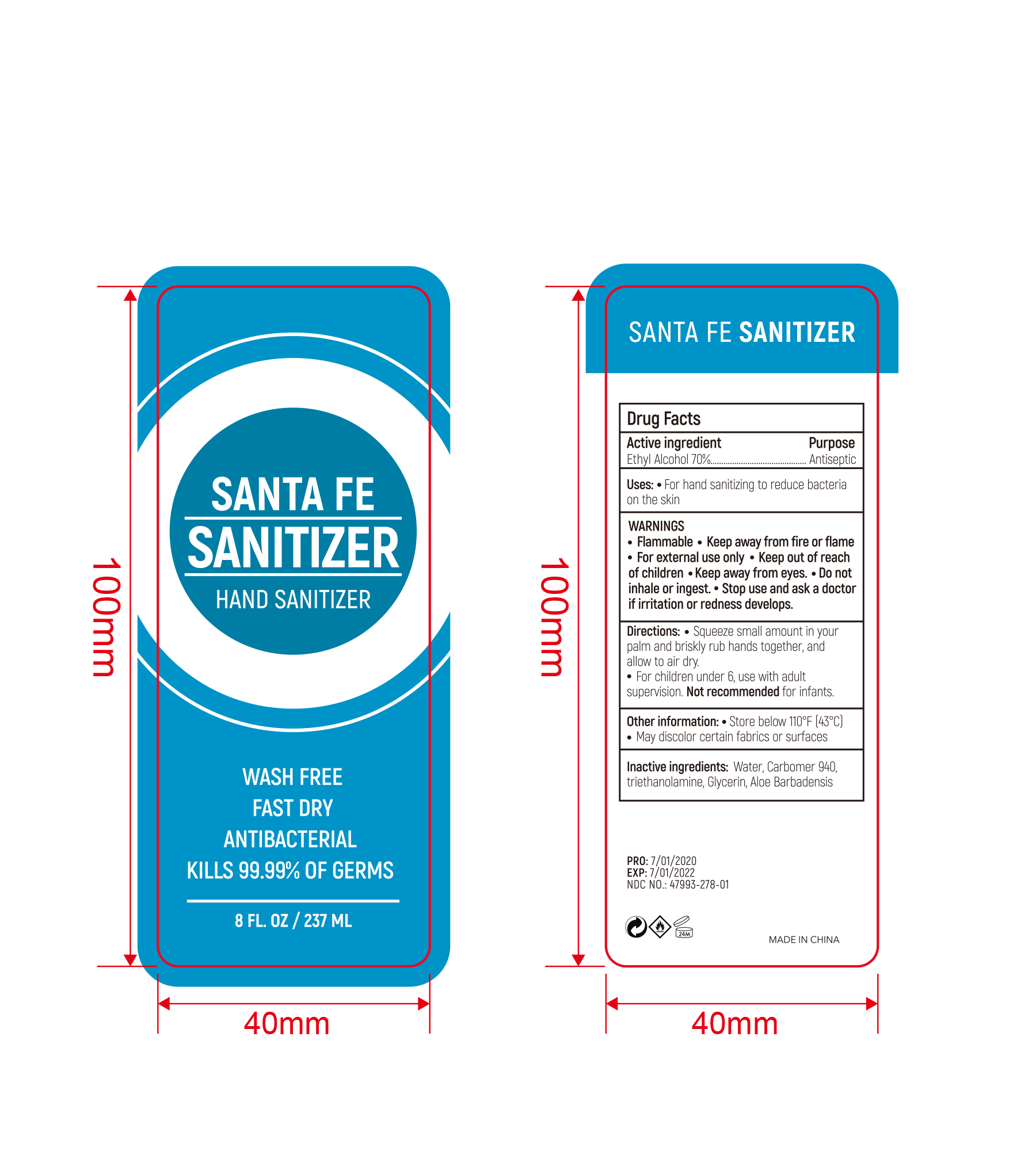 DRUG LABEL: HAND SANITIZER
NDC: 47993-278 | Form: GEL
Manufacturer: NINGBO JIANGBEI OCEAN STAR TRADING CO.,LTD
Category: otc | Type: HUMAN OTC DRUG LABEL
Date: 20201105

ACTIVE INGREDIENTS: ALCOHOL 70 g/112 mL
INACTIVE INGREDIENTS: CARBOMER 940; TRIETHANOLAMINE BENZOATE; ALOE VERA LEAF; WATER; GLYCERIN

47993-278

Active ingredients

Ethyl Alcohol 70%

PURPOSE

Antiseptic

Uses：

For hand sanitizing to reduce bacteria on the skin.

Warnings:

- Flammable.
- Keep away from fire or flame.
- For external use only.

- Keep out of reach of children.

WHEN USING

- Keep away from eyes.
- Do not inhale or ingest.

- Stop use and ask a doctor if irritation or redness develops.

Directions:

- Squeeze small amount in your palm and briskly rub hands together, and allow to air dry.
- For children under 6, use with adult supervision. Not recommended for infants.

Other information：

- Store below 110℉(43℃)
- May discolor certain fabrics or surfaces.

Inactive Ingredients:

Water,Carbomer 940,triethanolamine,Glycerin,Aloe Barbadensis